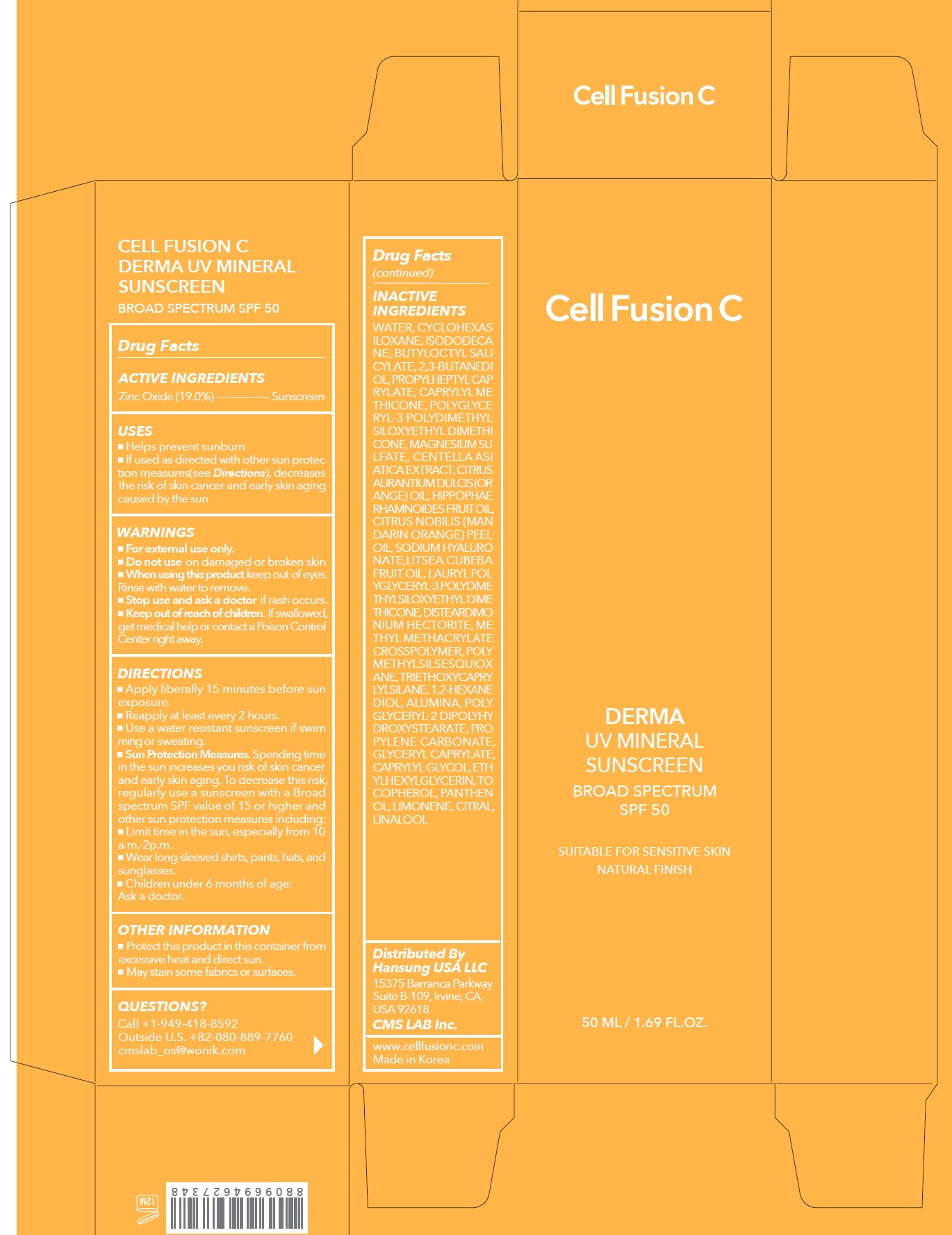 DRUG LABEL: Cell Fusion C Derma UV Mineral Sunscreen Broad Spectrum SPF 50
NDC: 52554-9064 | Form: CREAM
Manufacturer: CMS LAB Inc.
Category: otc | Type: HUMAN OTC DRUG LABEL
Date: 20250214

ACTIVE INGREDIENTS: ZINC OXIDE 19 g/50 mL
INACTIVE INGREDIENTS: BUTYLOCTYL SALICYLATE; CITRAL; LINALOOL; 2,3-BUTANEDIOL; DISTEARDIMONIUM HECTORITE; CAPRYLYL GLYCOL; SODIUM HYALURONATE; .ALPHA.-TOCOPHEROL, DL-; CYCLOHEXASILOXANE; ISODODECANE; TRIETHOXYCAPRYLYLSILANE; LAURYL POLYGLYCERYL-3 POLYDIMETHYLSILOXYETHYL DIMETHICONE (4000 MPA.S); WATER; CAPRYLYL METHICONE; CENTELLA ASIATICA; POLYMETHYLSILSESQUIOXANE; 1,2-HEXANEDIOL; ALUMINA; LIMONENE, (+)-; POLYGLYCERYL-3 POLYDIMETHYLSILOXYETHYL DIMETHICONE (4000 MPA.S); CITRUS AURANTIUM DULCIS (ORANGE) OIL; PROPYLENE CARBONATE; LITSEA CUBEBA FRUIT OIL; PANTHENOL; PROPYLHEPTYL CAPRYLATE; MAGNESIUM SULFATE; METHYL METHACRYLATE/GLYCOL DIMETHACRYLATE CROSSPOLYMER; POLYGLYCERYL-2 DIPOLYHYDROXYSTEARATE; GLYCERYL CAPRYLATE; ETHYLHEXYLGLYCERIN

52554-9064-1 Cell Fusion C Derma UV Mineral Sunscreen Broad Spectrum SPF 50 50mL

Drug Facts

ACTIVE INGREDIENTS

Zinc Oxide 19.0%

PURPOSE

Sunscreen

USES

- Helps prevent sunburn
- If used as directed with other sun protection measures (see Directions), decreases the risk of skin cancer and early skin aging caused by the sun

WARNINGS

For external use only

- Do not use on damaged or broken skin

- When using this product keep out of the eyes. Rinse with water to remove.

- Stop use and ask a doctor if rash occurs

- Keep out of reach of children. If swallowed, get medical help or contact a Poison Control Center right away.

DIRECTIONS

- Apply liberally 15 minutes before sun exposure.
- Reapply at least every 2 hours.
- Use a water resistant sunscreen if swimming or sweating.
- Sun Protection Measures. Spending time in the sun increases your risk of skin cancer and early skin aging. To decrease this risk, regularly use a sunscreen with a Broad Spectrum SPF value of 15 or higher and other sun protection measures including:

- Limit time in the sun, especially from 10 a.m.-2 p.m.
- Wear long-sleeved shirts, pants, hats, and sunglasses
- Children under 6 months of age: Ask a doctor.

OTHER INFORMATION

- Protect this product in this container from excessive heat and direct sun.
- May stain some fabrics or surfaces.

INACTIVE INGREDIENTS

Water, Cyclohexasiloxane, Isododecane, Butyloctyl Salicylate, 2,3-Butanediol, Propylheptyl Caprylate, Caprylyl Methicone, Polyglyceryl-3 Polydimethylsiloxyethyl Dimethicone, Magnesium Sulfate, Centella Asiatica Extract, Citrus Aurantium Dulcis (Orange) Oil, Hippophae Rhamnoides Fruit Oil, Citrus Nobilis (Mandarin Orange) Peel Oil, Sodium Hyaluronate, Litsea Cubeba Fruit Oil, Lauryl Polyglyceryl-3 Polydimethylsiloxyethyl Dimethicone, Disteardimonium Hectorite, Methyl Methacrylate Crosspolymer, Polymethylsilsesquioxane, Triethoxycaprylylsilane, 1,2-Hexanediol, Alumina, Polyglyceryl-2 Dipolyhydroxystearate, Propylene Carbonate, Glyceryl Caprylate, Caprylyl Glycol, Ethylhexylglycerin, Tocopherol, Panthenol, Limonene, Citral, Linalool

QUESTIONS?

Call +1-949-418-8592
Outside U.S. +82-080-889-7760
cmslab_os@wonik.com

Distributed By
Hansung USA LLC
15375 Barranca Parkway
Suite B-109, Irvine, CA USA 92618
CMS LAB Inc.
www.cellfusionc.com
Made in Korea

PRINCIPAL DISPLAY PANEL: 50 ML / 1.69 FL.OZ. Carton

Cell Fusion C

DERMA
UV MINERAL
SUNSCREEN
BROAD SPECTRUM
SPF 50
SUITABLE FOR SENSITIVE SKIN
NATURAL FINISH
50 ML / 1.69 FL.OZ.